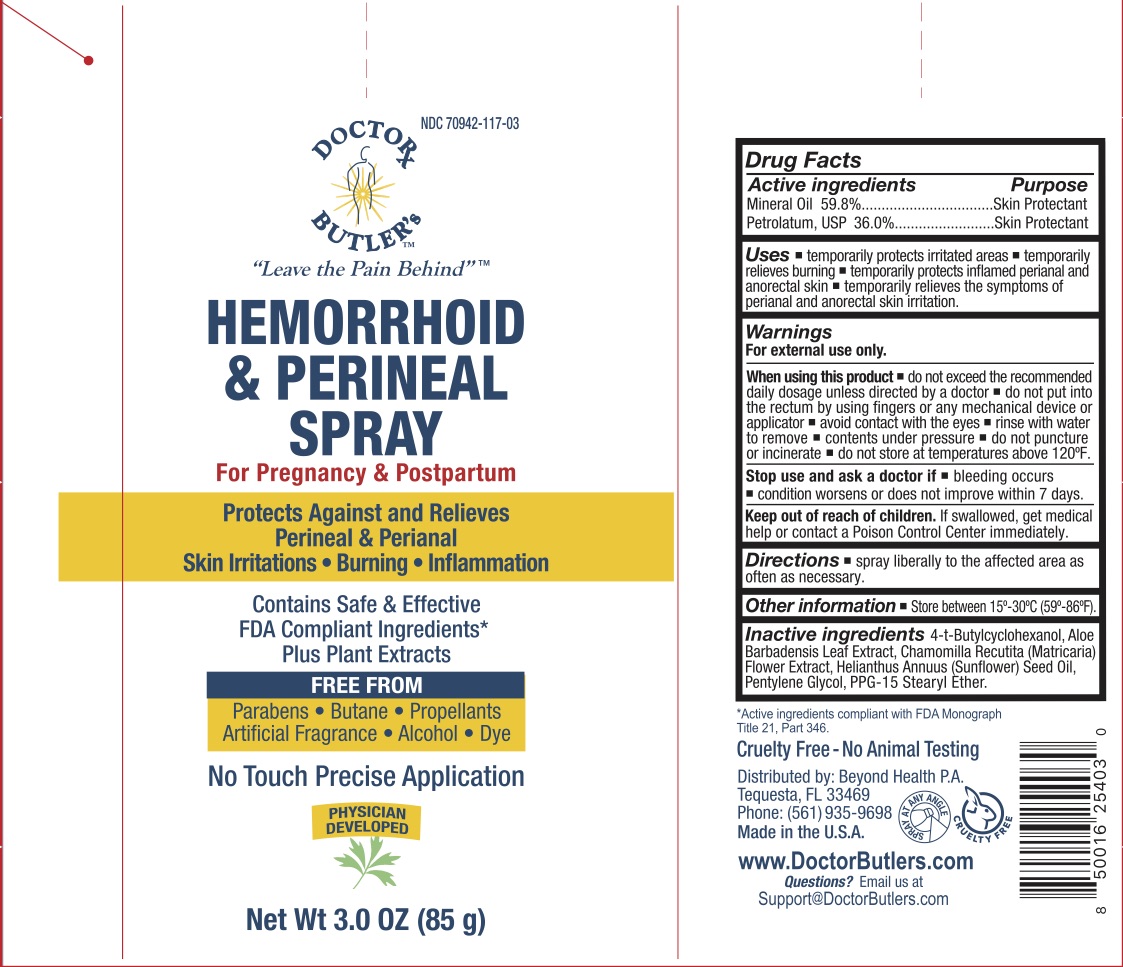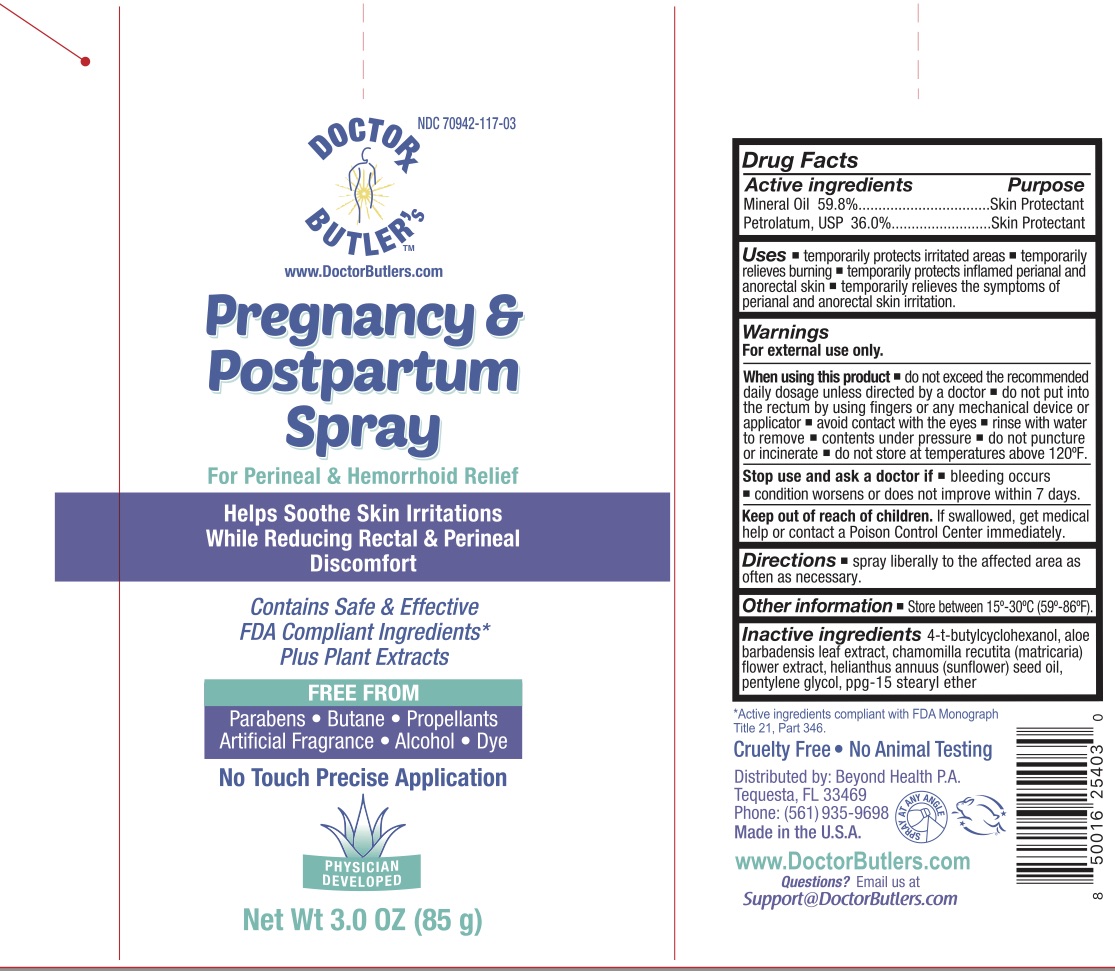 DRUG LABEL: Dr. Butler Hemorrhoid and Perineal
NDC: 70942-117 | Form: SPRAY
Manufacturer: Beyond Health P.A.
Category: otc | Type: HUMAN OTC DRUG LABEL
Date: 20250319

ACTIVE INGREDIENTS: MINERAL OIL 59.8 g/100 g
INACTIVE INGREDIENTS: PETROLATUM; PPG-15 STEARYL ETHER; ALOE; 4-TERT-BUTYLCYCLOHEXANOL; PENTYLENE GLYCOL; CHAMOMILE; SUNFLOWER OIL; POLYSORBATE 80; WATER

Dr. Butler Hemorrhoid and Perineal Spray

ACTIVE INGREDIENT

Mineral Oil 59.8%, Petrolatum 36%

PURPOSE

Skin Protectant

INDICATIONS AND USAGE

Temporarily protects and helps relieve chafed, chapped, or cracked skin.

WARNINGS

For external use only.

Do not use on deep or puncture wounds.

When using this product avoid contact in eyes, rinse with water to remove, contents under pressure, do not puncture or incinerate, do not store at temperatures above 120F.

Stop use and ask a doctor if condition worsens, symptoms last more than 7 days or clear up and occur again within a few days.

PREGNANCY OR BREAST FEEDING

Ask a healthcare or professional before use.

KEEP OUT OF REACH OF CHILDREN

If swallowed, seek medical help or contact a Poison Control Center immediately.

DOSAGE AND ADMINISTRATION

Spray liberally to the affected areas as often as necessary.

INACTIVE INGREDIENT

4-t-Butylcyclohexanol, Aloe Barbadensis Leaf Extract, Chamomilla Recutita (Matricaria) Flower Extract, Helianthus Annuus (Sunflower) Seed Oil, Pentylene Glycol, PPG-15 Stearyl Ether.